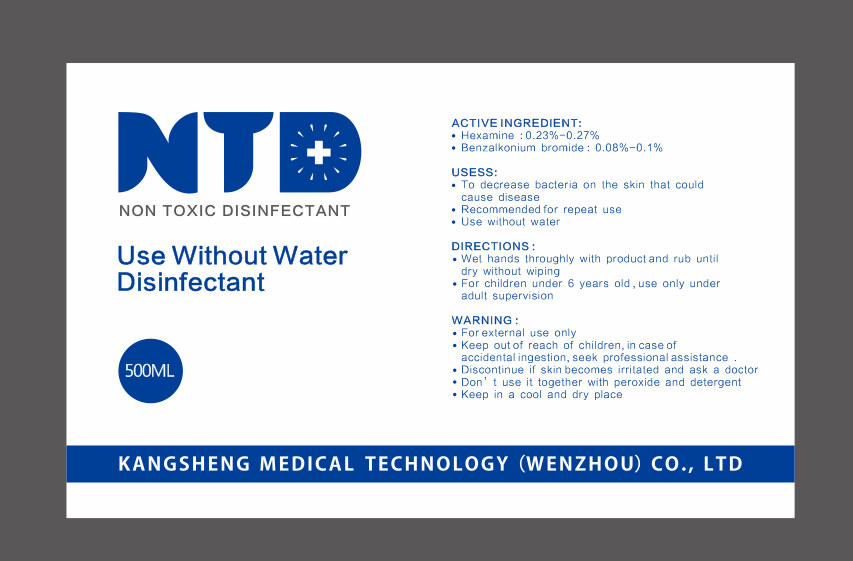 DRUG LABEL: SANITIZER
NDC: 93068-001 | Form: LIQUID
Manufacturer: KANGSHENG MEDICAL TECHNOLOGY (WENZHOU) CO. , LTD
Category: otc | Type: HUMAN OTC DRUG LABEL
Date: 20201126

ACTIVE INGREDIENTS: BENZALKONIUM BROMIDE 0.5 g/500 mL; METHENAMINE 1.35 g/500 mL
INACTIVE INGREDIENTS: WATER

ACTIVE INGREDIENT

Hexamine

Benzalkonium bromide

uses

To decrease bacteria on the skin that could cause disease
Recommended for repeat use

use without water

DIRECTIONS

Wel hands throughly with product and rub until dry without wiping

For children under 6 years old , use only under adult supervision

WARNINGS

For exlernal use only
Keep out of reach of children, in case of accidental ingestion,seek professional assistance
Discontinue if skin becomes irritaled and ask a doctor
Don' t use it together with peroxide and detergent
Keep in a cool and dry place

INACTIVE INGREDIENT

Deionized water

Keep out of reach of children

PURPOSE

Disinfection
Sterilization
No Rinseing